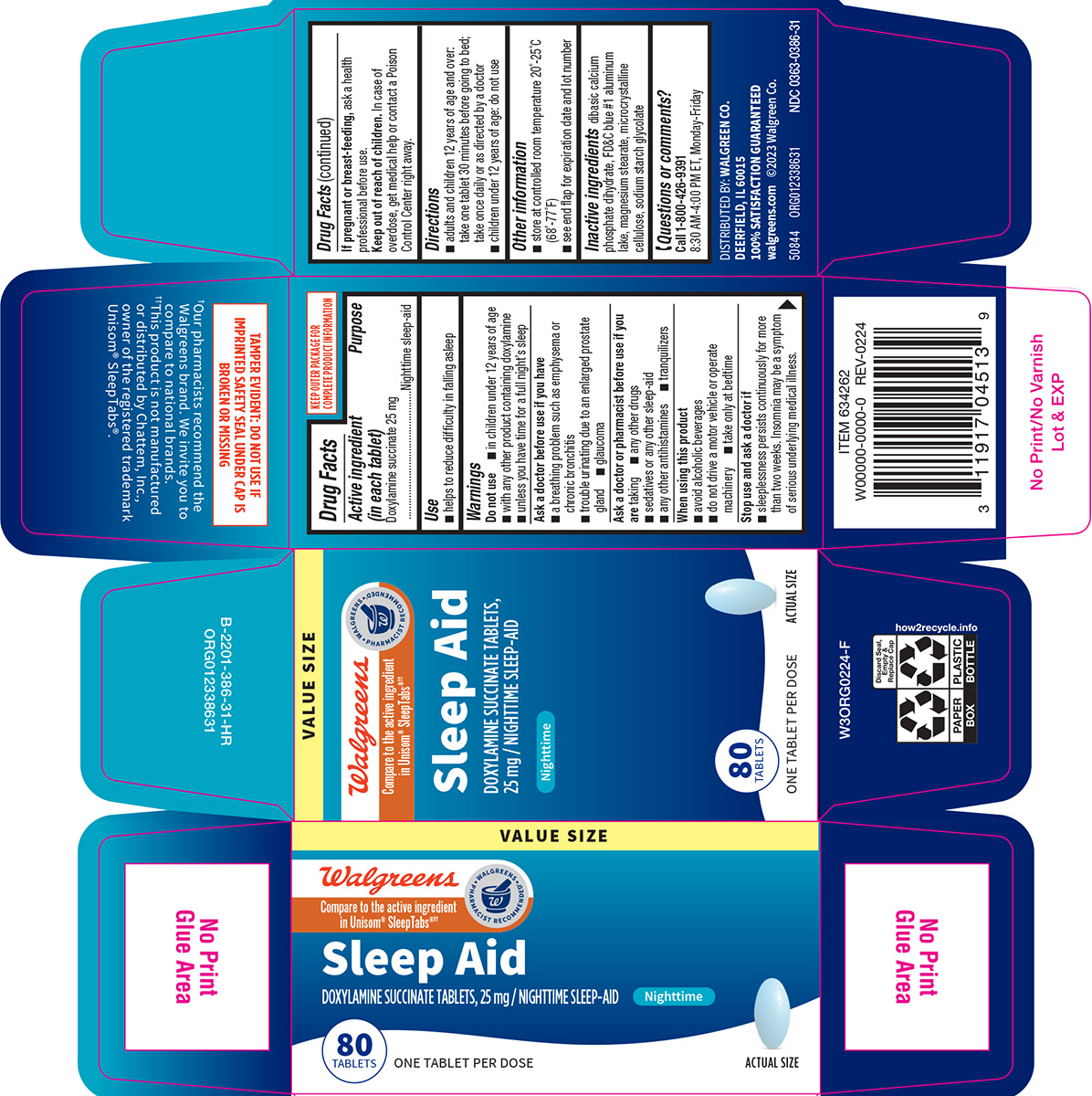 DRUG LABEL: Sleep Aid
NDC: 0363-0386 | Form: TABLET
Manufacturer: Walgreen Company
Category: otc | Type: HUMAN OTC DRUG LABEL
Date: 20260211

ACTIVE INGREDIENTS: DOXYLAMINE SUCCINATE 25 mg/1 1
INACTIVE INGREDIENTS: DIBASIC CALCIUM PHOSPHATE DIHYDRATE; FD&C BLUE NO. 1 ALUMINUM LAKE; MAGNESIUM STEARATE; MICROCRYSTALLINE CELLULOSE; SODIUM STARCH GLYCOLATE TYPE A POTATO

Walgreens 44-386

Active ingredient (in each tablet)

Doxylamine succinate 25 mg

Purpose

Nighttime sleep-aid

Use

- helps to reduce difficulty in falling asleep

Warnings

Do not use

- in children under 12 years of age
- with any other product containing doxylamine
- unless you have time for a full night’s sleep

Ask a doctor before use if you have

- a breathing problem such as emphysema or chronic bronchitis
- trouble urinating due to an enlarged prostate gland
- glaucoma

Ask a doctor or pharmacist before use if you are

taking

- any other drugs
- sedatives or any other sleep-aid
- any other antihistamines
- tranquilizers

When using this product

- avoid alcoholic beverages
- do not drive a motor vehicle or operate machinery
- take only at bedtime

Stop use and ask a doctor if

- sleeplessness persists continuously for more than two weeks. Insomnia may be a symptom of serious underlying medical illness.

If pregnant or breast-feeding,

ask a health professional before use.

Keep out of reach of children.

In case of overdose, get medical help or contact a Poison Control Center right away.

Directions

- adults and children 12 years of age and over: take one tablet 30 minutes before going to bed; take once daily or as directed by a doctor
- children under 12 years of age: do not use

Other information

- store at controlled room temperature 20°-25°C (68°-77°F)
- see end flap for expiration date and lot number

Inactive ingredients

dibasic calcium phosphate dihydrate, FD&C blue #1 aluminum lake, magnesium stearate, microcrystalline cellulose, sodium starch glycolate

Questions or comments?

Call 1-800-426-9391 8:30 AM-4:00 PM ET, Monday-Friday

Principal display panel

VALUE SIZE

Walgreens

WALGREENS PHARMACIST RECOMMENDED†

Compare to the active ingredient
in Unisom® SleepTabs®††

Sleep Aid
DOXYLAMINE SUCCINATE TABLETS,
25 mg / NIGHTTIME SLEEP-AID
Nighttime

80
TABLETS

ONE TABLET PER DOSE

ACTUAL SIZE

TAMPER EVIDENT: DO NOT USE IF
IMPRINTED SAFETY SEAL UNDER CAP IS
BROKEN OR MISSING

†Our pharmacists recommend the
Walgreens brand. We invite you to
compare to national brands.
††This product is not manufactured
or distributed by Chattem, Inc.,
owner of the registered trademark
Unisom® SleepTabs®.

DISTRIBUTED BY: WALGREEN CO.
DEERFIELD, IL 60015
100% SATISFACTION GUARANTEED
walgreens.com ©2023 Walgreen Co.

50844 ORG012338631

NDC 0363-0386-31

WALGREENS 44-386